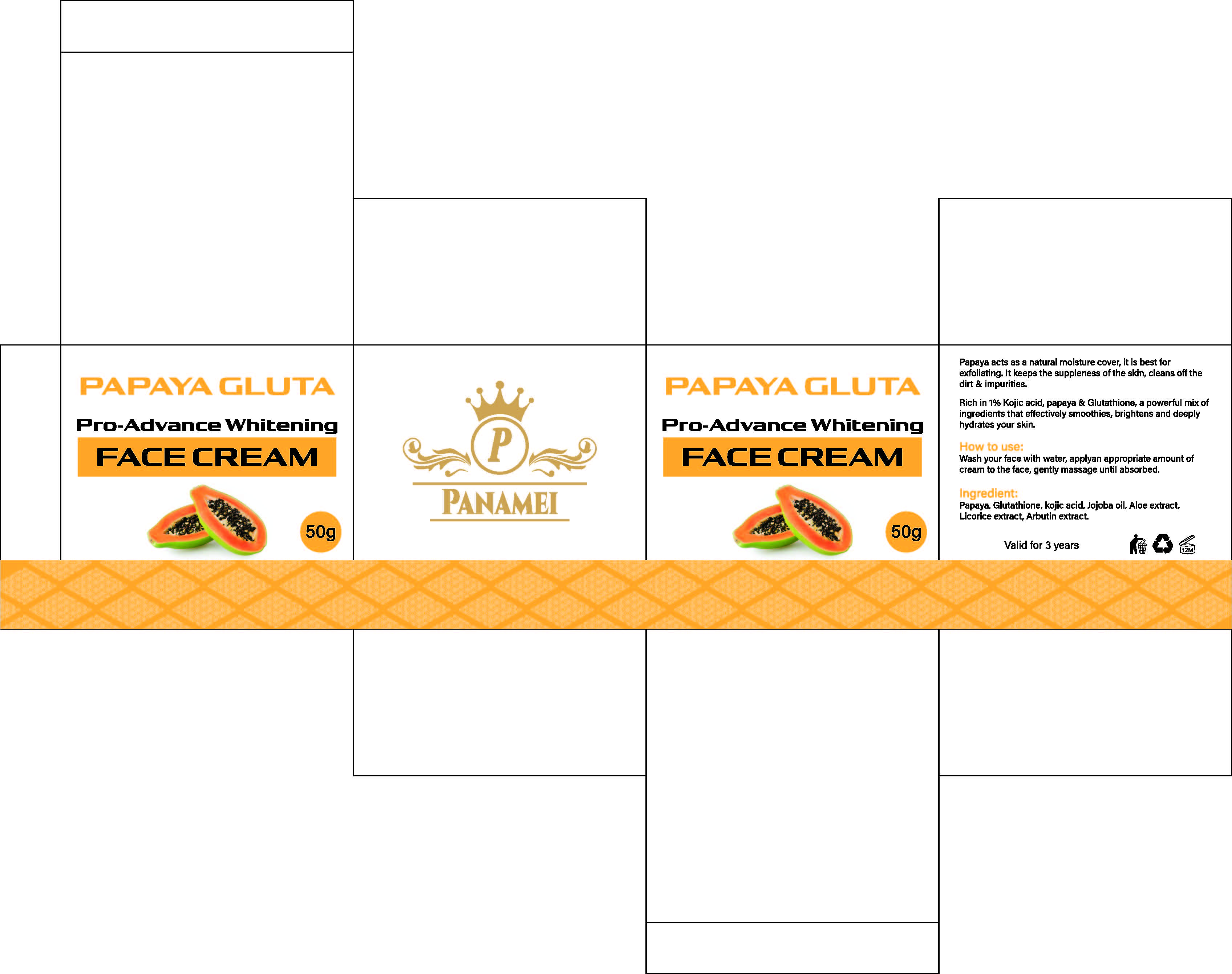 DRUG LABEL: Super lightening Based on gold 24k and kojic acid Cream
NDC: 84423-080 | Form: CREAM, AUGMENTED
Manufacturer: Guangzhou Kadiya Biotechnology Co., Ltd.
Category: otc | Type: HUMAN OTC DRUG LABEL
Date: 20250526

ACTIVE INGREDIENTS: PAPAYA 1 g/50 g
INACTIVE INGREDIENTS: CI 19140; GLYCERYL STEARATE; TRIETHANOLAMINE; MYRISTIC ACID; LAURIC ACID; MINERAL OIL; PALMITIC ACID; TITANIUM DIOXIDE; ALUMINA; WATER; PEG-60 SORBITAN STEARATE; PEG-75 LANOLIN; METHYLPARABEN; DIMETHICONE; GLYCERIN; CETYLPYRIDINIUM BROMIDE; ALPHA-ARBUTIN; NIACINAMIDE; ETHOXYDIGLYCOL; PHENOXYETHANOL; ALLANTOIN; NUTMEG; SODIUM CHLORIDE; CI 15985; STEAROLIC ACID; PROPYLPARABEN

PURPOSE

For Facial Skin Moisturizing, Antioxidant, Blemish Removal, Whitening, Brightening

INACTIVE INGREDIENT

AQUA，MINERAL OIL，GLYCERIN，Polyethylene，PROPYLENE GLYCOL，STEARYL ALCOHOL，BUTYLENE GLYCOL，Steareth-2，Steareth-21，CETYL ALCOHOL，DIMETHICONE，Isosorbide Dimethyl Ether，GLYCERYL STEARATE，PEG-100，PHENOXYETHANOL，ALLANTOIN，Polyacrylamide，ALOE BARBADENSIS LEAF EXTRACT，ANTHEMIS NOBILIS FLOWER EXTRACT，PORTULACA OLERACEA FLOWER/LEAF/STEM EXTRACT，PELARGONIUM GRAVEOLENS FLOWER/LEAF/STEM EXTRACT，XANTHAN GUM，FRAGRANCE，ETHYLHEXYLGLYCERIN， C13-14 Isoparaffin，DISODIUM EDTA，Laureth-7

WARNINGS

1.Before use, perform a skin test on your arm and discontinue use if you have allergy symptoms or skin abnormalities.

2、For external use only, avoid contact with eyes when used

3、Keep out of reach of children

INDICATIONS AND USAGE

Wash vour face with water, applvan appropriate amount ofcream to the face, gently massage until absorbed.

DOSAGE AND ADMINISTRATION

Gently apply a little bit with your hands, and then spread it evenly.

KEEP OUT OF REACH OF CHILDREN SECTION

ACTIVE INGREDIENT

CARICA PAPAYA FRUIT EXTRACT

PACKAGE LABEL

Active Ingredients
CARICA PAPAYA FRUIT EXTRACT

Uses：
For Facial Skin Moisturizing, Antioxidant, Blemish Removal, Whitening, Brightening
The storage method：
Store sealed in a cool place and out of sunlight

Warning.
1.Before use, perform a skin test on your arm and discontinue use if you have allergy symptoms or skin abnormalities.
2、For external use only, avoid contact with eyes when used
3、Keep out of reach of children

Inactive ingredients：
AQUA，MINERAL OIL，GLYCERIN，Polyethylene，PROPYLENE GLYCOL，STEARYL ALCOHOL，BUTYLENE GLYCOL，Steareth-2，Steareth-21，CETYL ALCOHOL，DIMETHICONE，Isosorbide Dimethyl Ether，GLYCERYL STEARATE，PEG-100，PHENOXYETHANOL，ALLANTOIN，Polyacrylamide，ALOE BARBADENSIS LEAF EXTRACT，ANTHEMIS NOBILIS FLOWER EXTRACT，PORTULACA OLERACEA FLOWER/LEAF/STEM EXTRACT，PELARGONIUM GRAVEOLENS FLOWER/LEAF/STEM EXTRACT，XANTHAN GUM，FRAGRANCE，ETHYLHEXYLGLYCERIN， C13-14 Isoparaffin，DISODIUM EDTA，Laureth-7